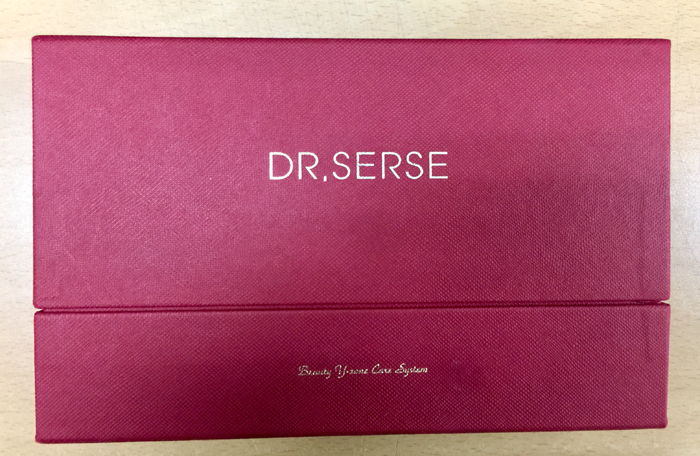 DRUG LABEL: DR.SERSE Serum
NDC: 71540-0001 | Form: GEL
Manufacturer: T.S international
Category: otc | Type: HUMAN OTC DRUG LABEL
Date: 20200109

ACTIVE INGREDIENTS: GLYCERIN 1 g/100 mL
INACTIVE INGREDIENTS: WATER; HUMAN ADIPOSE; BUTYLENE GLYCOL

Drug Facts

ACTIVE INGREDIENT

GLYCERIN

INACTIVE INGREDIENT

Water
Human Adipose Stromal Cell Conditioned Media Extract
Butylene Glycol
Hydroxyethyl Acrylate/Sodium Acryloyldimethyl Taurate Copolymer
Aspalathus Linearis Extract
Saccharomyces/Viscum Album (Mistletoe) Ferment Extract
Lactobacillus/Soybean Ferment Extract
Saccharomyces/Imperata Cylindrica Root Ferment Extract
Artemisia Capillaris Extract
Rosmarinus Officinalis (Rosemary) Leaf Extract
Sophora Angustifolia Root Extract
rh-Oligopeptide-1
Acetyl Hexapeptide-8
Copper Tripeptide-1
Lavandula Angustifolia (Lavender) Oil
Simmondsia Chinensis (Jojoba) Seed Oil
Squalane
Lecithin
Sodium Ascorbyl Phosphate
Polysorbate 20
Hydroxyethylcellulose
Algin
Xanthan Gum
Menthol
Allantoin
Lactic Acid
Citric Acid
Hydrogenated Lecithin
PEG-60 Hydrogenated Castor Oil
Disodium EDTA
Potassium Hydroxide
Ethylhexylglycerin
1,2-Hexanediol
Chlorphenesin

PURPOSE

Skin protectant

keep out of reach of the children

INDICATIONS AND USAGE

1.Take out appropriate amount of this serum on the hand
2.spread it evenly on the skin.
3.Massage gently in the skin.
4.fully absorbs the product.

WARNINGS

•Precautions when using

1. After using or using cosmetics, consult a specialist if you have any abnormal symptoms such as red spots, swelling or itching or side effects caused by direct sunlight.

2. Do not use on wounded area

3. storage and handling Precautions

a) Keep out of the reach of children

b) Store away from direct sunlight.

DOSAGE AND ADMINISTRATION

for external use only